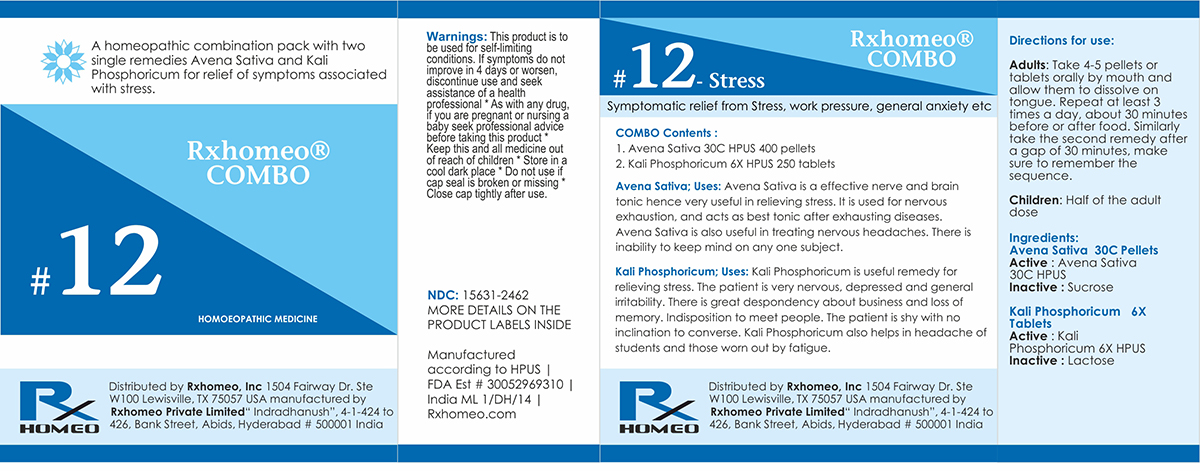 DRUG LABEL: Rxhomeo Homeopathic Combo 12
NDC: 15631-2462 | Form: KIT | Route: ORAL
Manufacturer: Rxhomeo Private Limited d.b.a.
Category: homeopathic | Type: HUMAN OTC DRUG LABEL
Date: 20161023

ACTIVE INGREDIENTS: AVENA SATIVA FLOWERING TOP 1 [hp_X]/1 1; POTASSIUM PHOSPHATE, DIBASIC 1 [hp_X]/1 1
INACTIVE INGREDIENTS: SUCROSE; LACTOSE

ACTIVE INGREDIENT

AVENA SATIVA HPUS 1X and higher

KALI PHOSPHORICUM HPUS 1X and higher

USES

A homeopathic combination pack with two single remedies Avena Sativa and Kali Phosphoricum for relief of symptoms associated with stress.

Avena Sativa: Avena Sativa is a effective nerve and brain tonic hence very useful in relieving stress. It is used for nervous exhaustion, and acts as best tonic after exhausting diseases. Avena Sativa is also useful in treating nervous headaches. There is inability to keep mind on any one subject.

Kali Phosphoricum: Kali Phosphoricum is useful remedy for relieving stress. The patient is very nervous, depressed and general irritability. There is great despondency about business and loss of memory. Indisposition to meet people. The patient is shy with no inclination to converse. Kali Phosphoricum also helps in headache of students and those worn out by fatigue.

INDICATIONS

Condition listed above or as directed by the physician

DOSAGE

Adults: Take 4-5 pellets or tablets orally by mouth and allow them to dissolve on tongue. Repeat at least 3 times a day, about 30 minutes before or after food. Similarly take the second remedy after a gap of 30 minutes, make sure to remember the sequence.

Children: Half of the adult dose.

WARNINGS

This product is to be used for self-limiting conditions

STOP USE

If symptoms do not improve in 4 days, or worsen, discontinue use and seek assistance of health professional

KEEP OUT OF REACH OF CHILDREN

Keep this and all medication out of reach of children

Do not use if capseal is broken or missing.

Close the cap tightly after use.

INACTIVE INGREDIENTS

Sucrose for Pellets.

Lactose for Tablets.

STORAGE

Store in a cool dark place

QUESTIONS OR COMMENTS

www.Rxhomeo.com | 1.888.2796642 | info@rxhomeo.com
Rxhomeo, Inc 1504 Fairway Dr. Ste W 100 Lewisville, TX 75057 USA